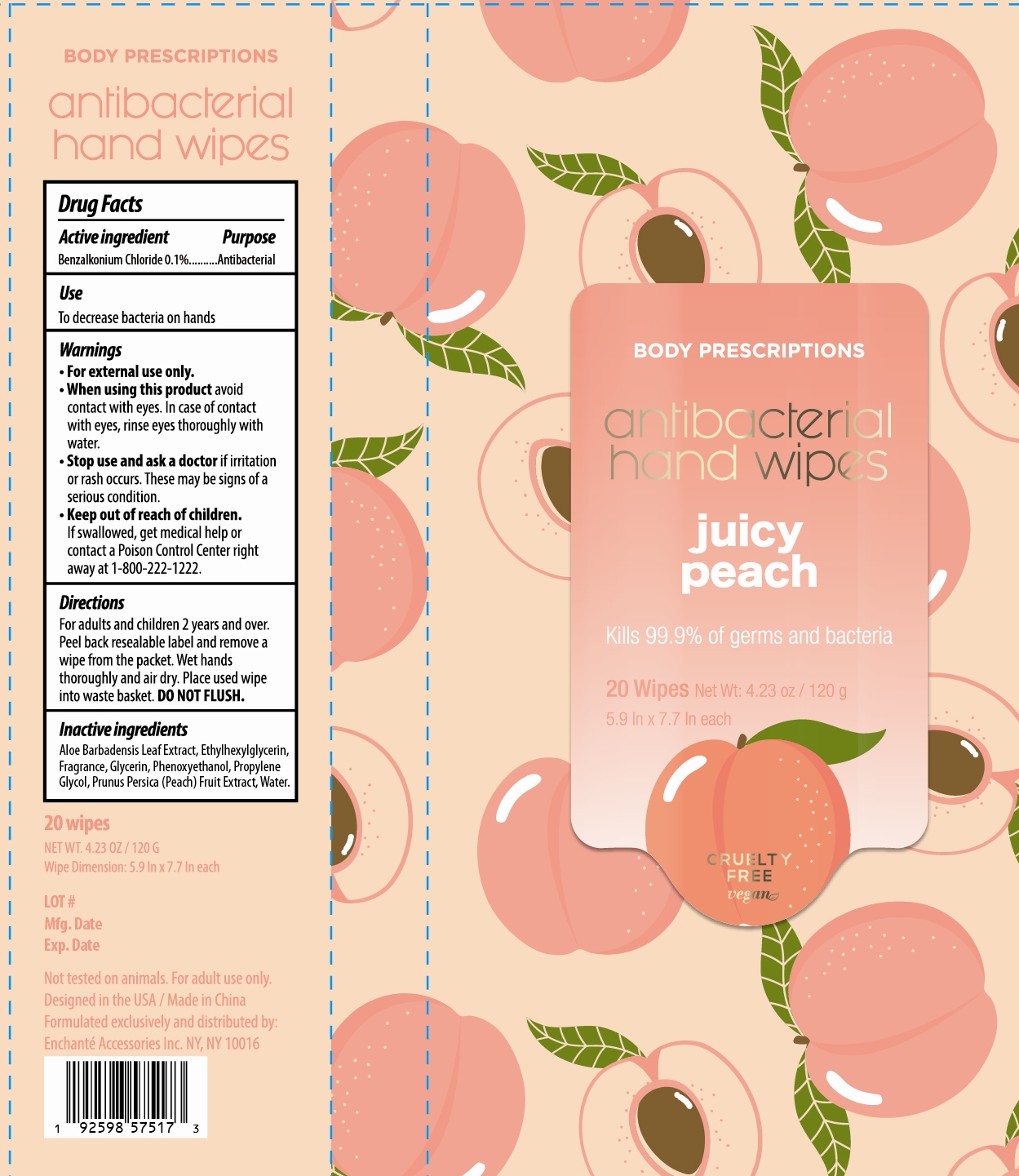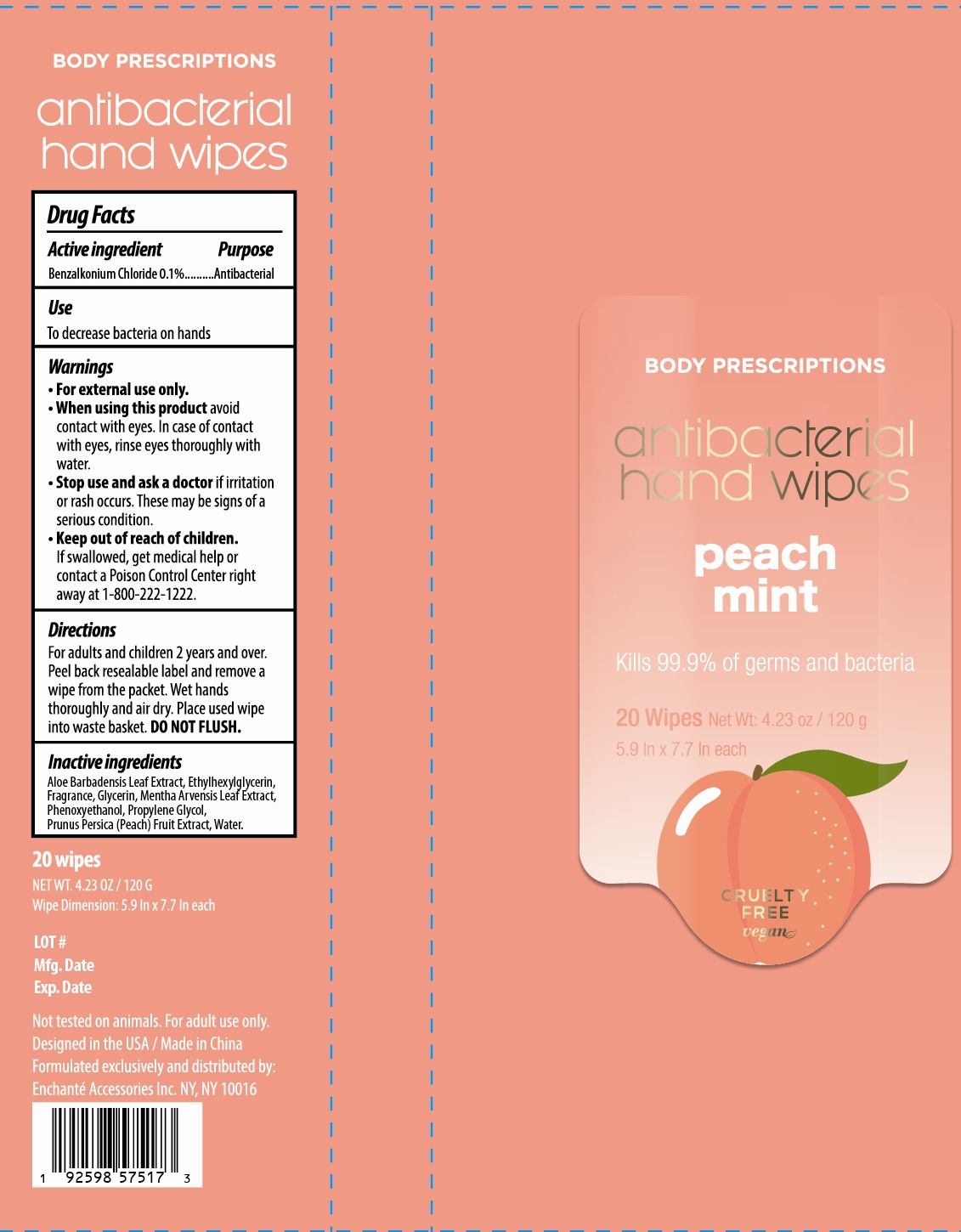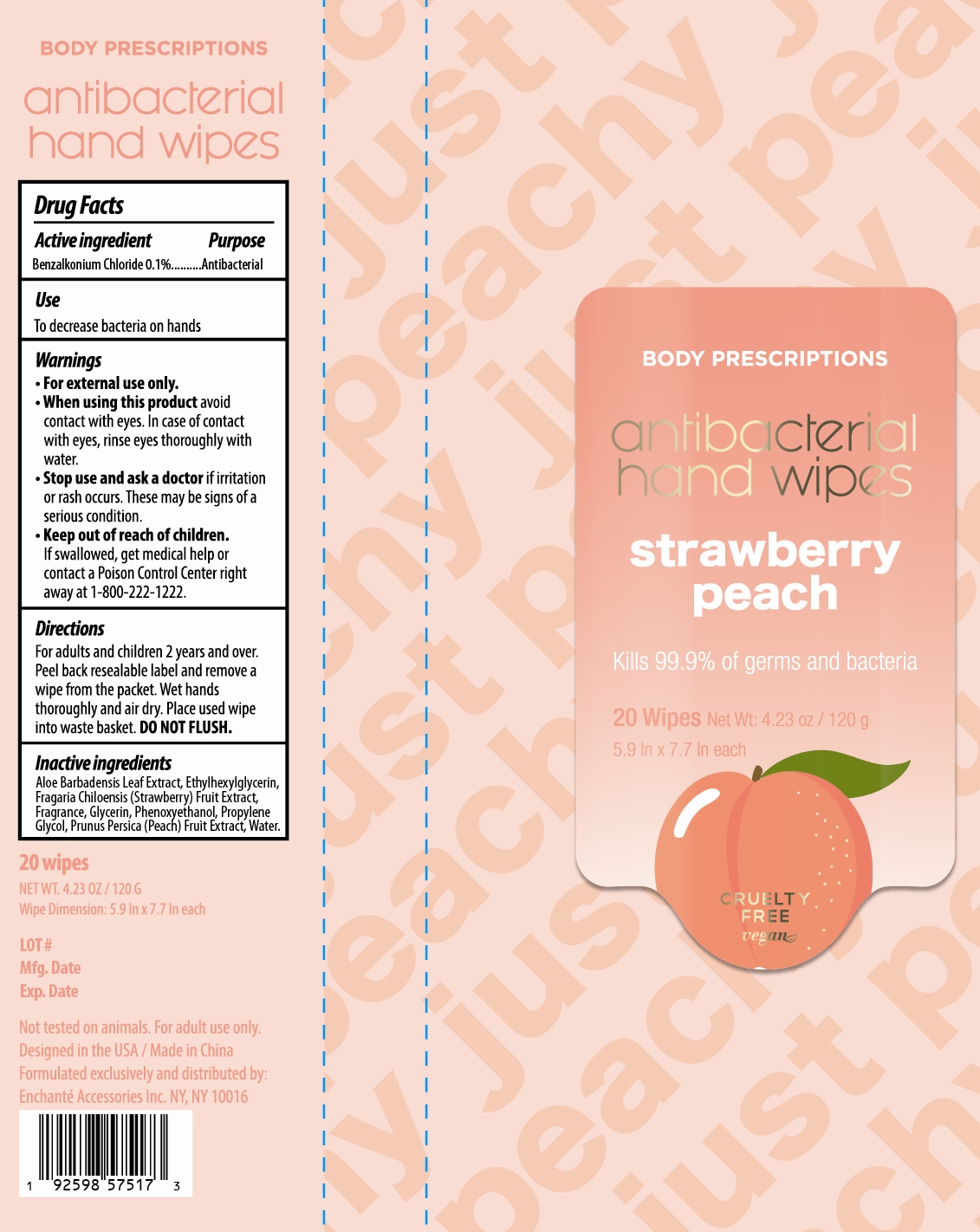 DRUG LABEL: BODY PRESCRIPTIONS antibacterial hand wipes juicy peach peach mint strawberry peach
NDC: 50563-375 | Form: KIT | Route: TOPICAL
Manufacturer: ENCHANTE ACCESSORIES INC.
Category: otc | Type: HUMAN OTC DRUG LABEL
Date: 20201027

ACTIVE INGREDIENTS: BENZALKONIUM CHLORIDE 4.5 mg/1 1; BENZALKONIUM CHLORIDE 4.5 mg/1 1; BENZALKONIUM CHLORIDE 4.5 mg/1 1
INACTIVE INGREDIENTS: WATER; GLYCERIN; ETHYLHEXYLGLYCERIN; PHENOXYETHANOL; PROPYLENE GLYCOL; ALOE VERA LEAF; PEACH JUICE; WATER; GLYCERIN; ETHYLHEXYLGLYCERIN; PHENOXYETHANOL; PROPYLENE GLYCOL; ALOE VERA LEAF; PEACH JUICE; MENTHA ARVENSIS LEAF; WATER; GLYCERIN; ETHYLHEXYLGLYCERIN; PHENOXYETHANOL; PROPYLENE GLYCOL; ALOE VERA LEAF; PEACH JUICE; STRAWBERRY JUICE

50563-372/373/374/375 G1ABCW09

BODY PRESCRIPTIONS antibacterial hand wipes juicy peach

Active Ingredient

Benzalkonium Chloride 0.1%

Purpose

Antibacterial

Use

■ To decrease bacteria on hands

WARNINGS

For external use only

When using this product avoid contact with eyes. In case of contact with eyes, rinse thoroughly with water

Stop use and ask a doctor if irritation or rash occurs. This may be signs of a serious condition

Keep out of reach of children. If swallowed, get medical help or contact a Poison Control Center right away at 1-800-222-1222

Directions

For adults and children two years and over

Peel over reusable label and remove a wipe from the packet.

Wet hands thoroughly and air dry.

Place used wipes into waste basket. Do not flush.

Inactive ingredients

Aloe Barbadensis Leaf Extract, Ethylhexylglycerin, Fragrance, Glycerin, Phenoxyethanol, Propylene Glycol, Prunus Persica (Peach) Fruit Extract, Water

BODY PRESCRIPTIONS antibacterial hand wipes peach mint

Active Ingredient

Benzalkonium Chloride 0.1%

Purpose:

Antibacterial

Uses:

■ To decrease bacteria on hands

Warnings

For external use only

When using this product avoid contact with eyes. In case of contact with eyes, rinse thoroughly with water

Stop use and ask a doctor if irritation or rash occurs. This may be signs of a serious condition

Keep out of reach of children. If swallowed, get medical help or contact a Poison Control Center right away at 1-800-222-1222

Directions

For adults and children two years and over

Peel over reusable label and remove a wipe from the packet.

Wet hands thoroughly and air dry.

Place used wipes into waste basket. Do not flush.

Inactive Ingredients

Aloe Barbadensis Leaf Extract, Ethylhexylglycerin, Fragrance, Glycerin, Mentha Arvensis Leaf Extract, Phenoxyethanol, Propylene Glycol, Prunus Persica (Peach) Fruit Extract, Water

BODY PRESCRIPTIONS antibacterial hand wipes strawberry peach

Active Ingredient

Benzalkonium Chloride 0.1%

Purpose

Antibacterial

Uses

■ To decrease bacteria on hands

Warnings

For external use only

When using this product avoid contact with eyes. In case of contact with eyes, rinse thoroughly with water

Stop use and ask a doctor if irritation or rash occurs. This may be signs of a serious condition

Keep out of reach of children. If swallowed, get medical help or contact a Poison Control Center right away at 1-800-222-1222

Directions

For adults and children two years and over

Peel over reusable label and remove a wipe from the packet.

Wet hands thoroughly and air dry.

Place used wipes into waste basket. Do not flush.

Inactive Ingredients

Aloe Barbadensis Leaf Extract, Ethylhexylglycerin, Fragaria Chiloensis (Strawberry) Fruit Extract, Fragrance, Glycerin, Phenoxyethanol, Propylene Glycol, Prunus Persica (Peach) Fruit Extract, Water